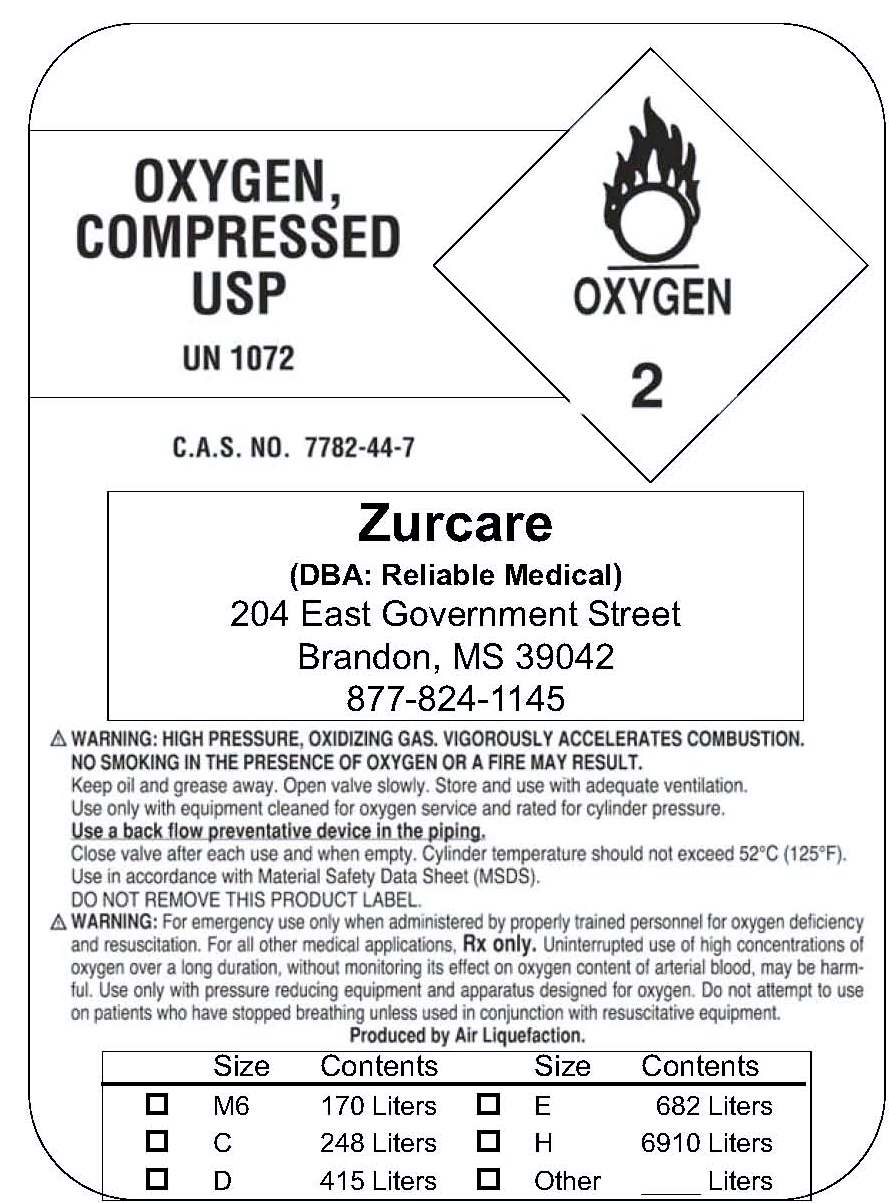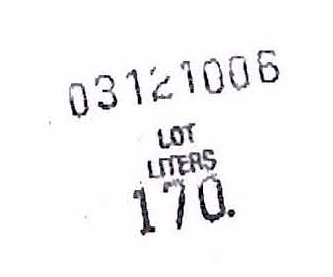 DRUG LABEL: Oxygen
NDC: 50825-001 | Form: GAS
Manufacturer: Zurcare dba Reliable Medical
Category: prescription | Type: HUMAN PRESCRIPTION DRUG LABEL
Date: 20100614

ACTIVE INGREDIENTS: Oxygen 99 L/100 L

Oxygen